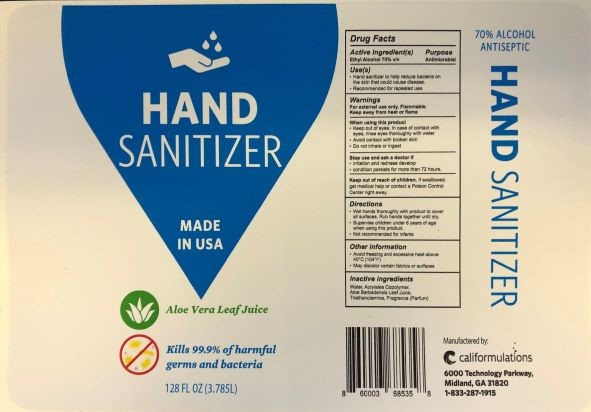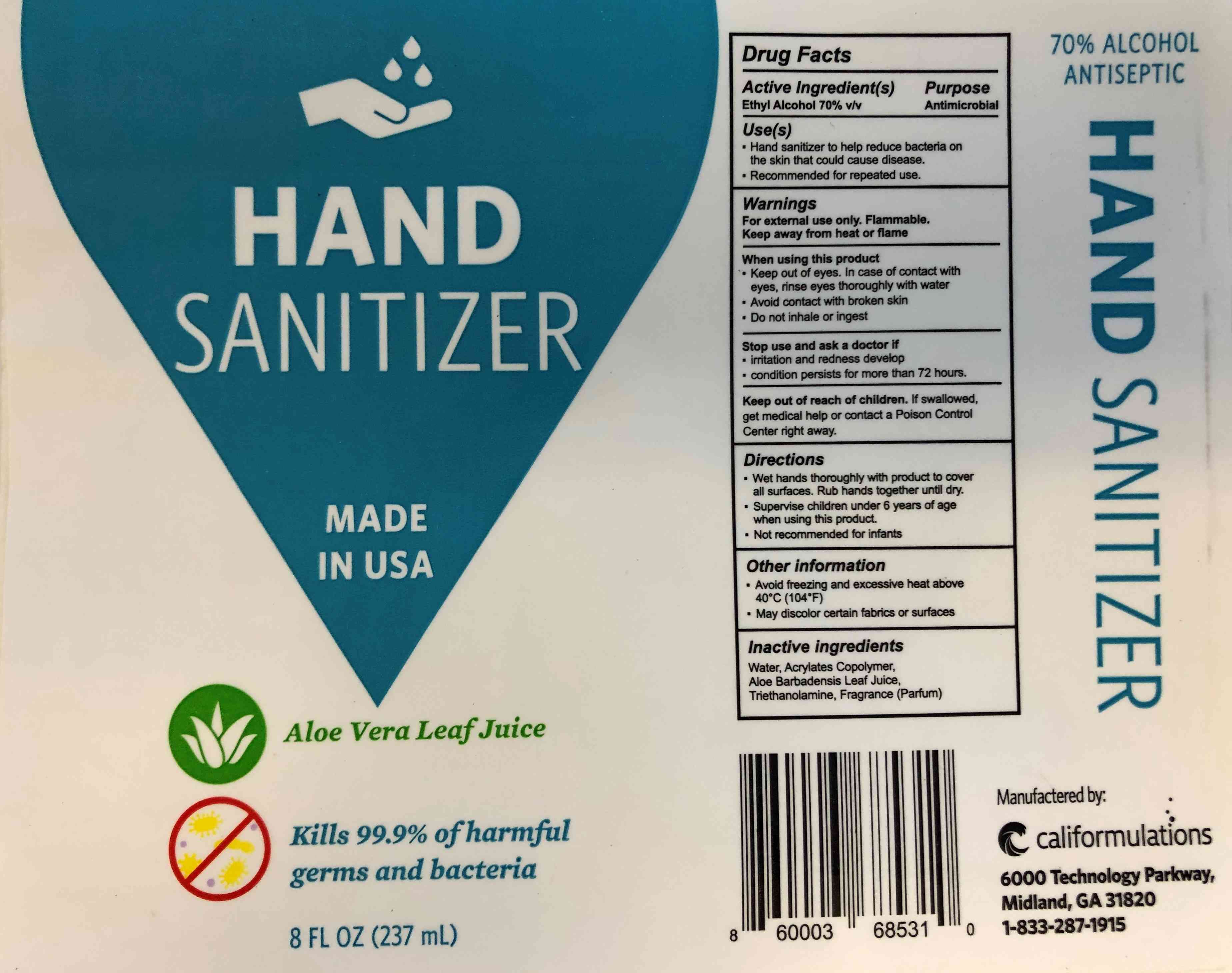 DRUG LABEL: Hand Sanitizer Gel
NDC: 74391-003 | Form: GEL
Manufacturer: Califormulations LLC
Category: otc | Type: HUMAN OTC DRUG LABEL
Date: 20200806

ACTIVE INGREDIENTS: ALCOHOL 70 mL/100 mL
INACTIVE INGREDIENTS: TRIETHYLAMINE; ALOE VERA LEAF; WATER; METHACRYLIC ACID - ETHYL ACRYLATE COPOLYMER (4500 MPA.S)

Hand Sanitizer Gel

Active Ingredient

Alcohol 70% v/v. Purpose: Antiseptic

Purpose

Antiseptic, Hand Sanitizer

Use

Hand Sanitizer to help reduce bacteria on the skin that could cause disease. Recommended for repeated use.

Warnings

For external use only. Flammable. Keep away from heat or flame

When using this product

- Keep out of eyes. In case of contact with eyes, rinse eyes thoroughly with water
- Avoid contact with broken skin
- Do not inhale or ingest

Stop use and ask a doctor if

- irritation and redness develop
- condition persist for more than 72 hours

Keep out of reach of children. If swallowed, get medical help or contact a Poison Control Center right away.

Directions

- Wet hands thoroughly wit product to cover all surfaces. Rub hands together until dry.
- Supervise children under 6 years of age when using this product.
- Not recommended for infants.

Other information

- Avoid freezing and excessive heat above 40C (104F)
- May discolor certain fabrics or surfaces

Inactive ingredients

Water, Acrylates Copolymer, Aloe Barbadensis Leaf Juice, Triethanolamine, Frangrance (Parfum)

Package Label - Principal Display Panel

3785 mL NDC: 74391-003-01

237 mL NDC: 74391-003-08